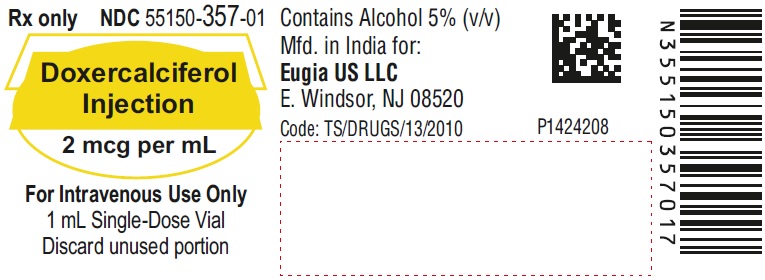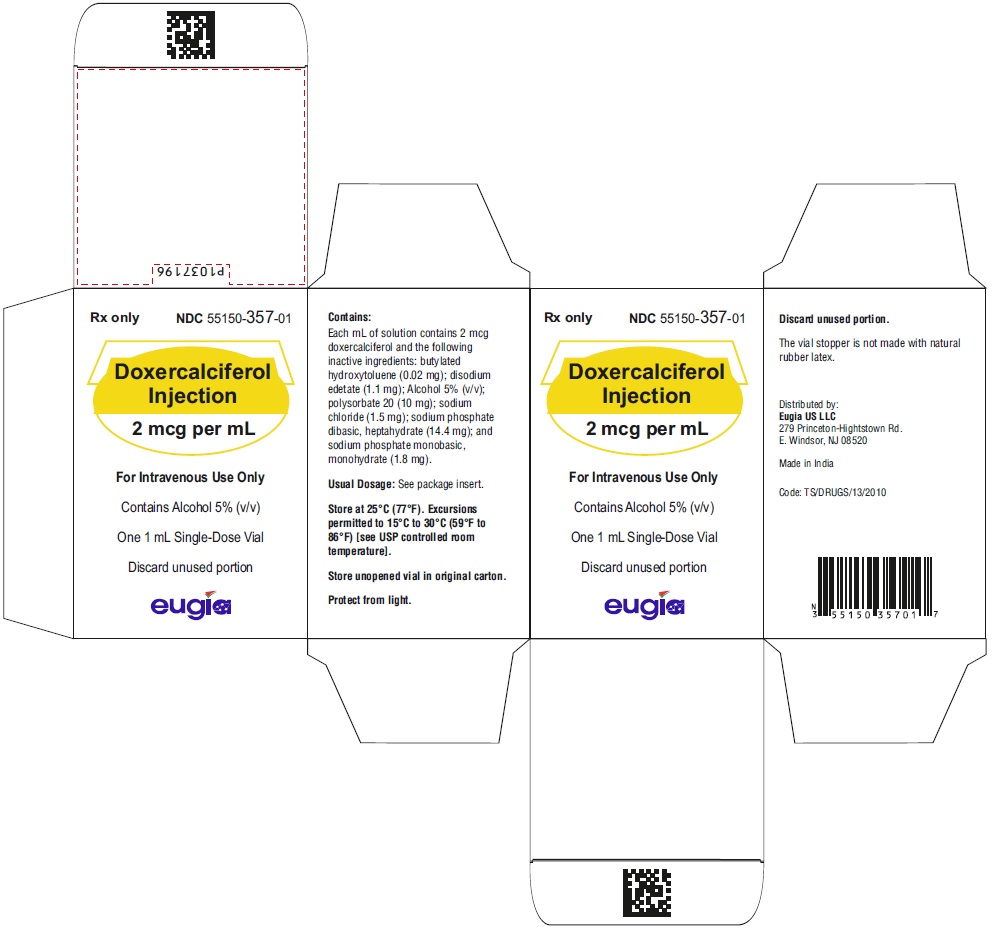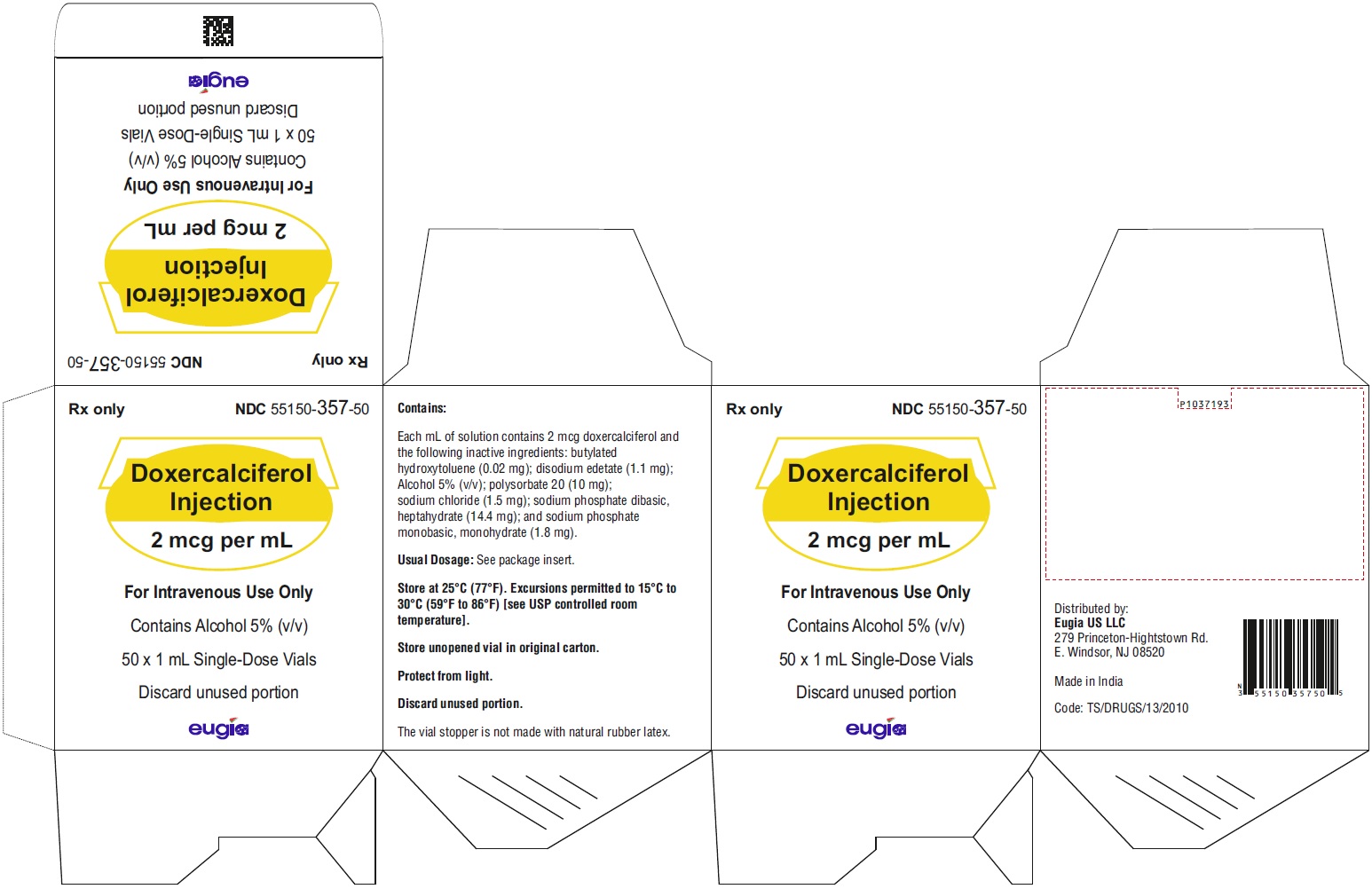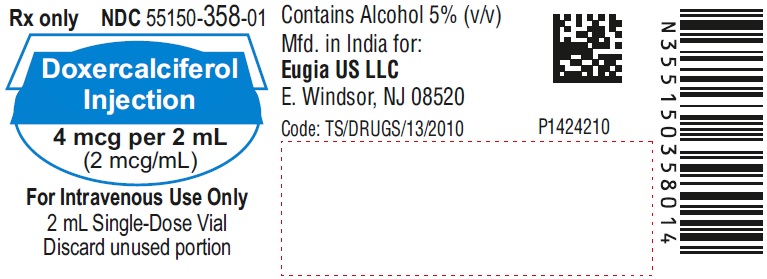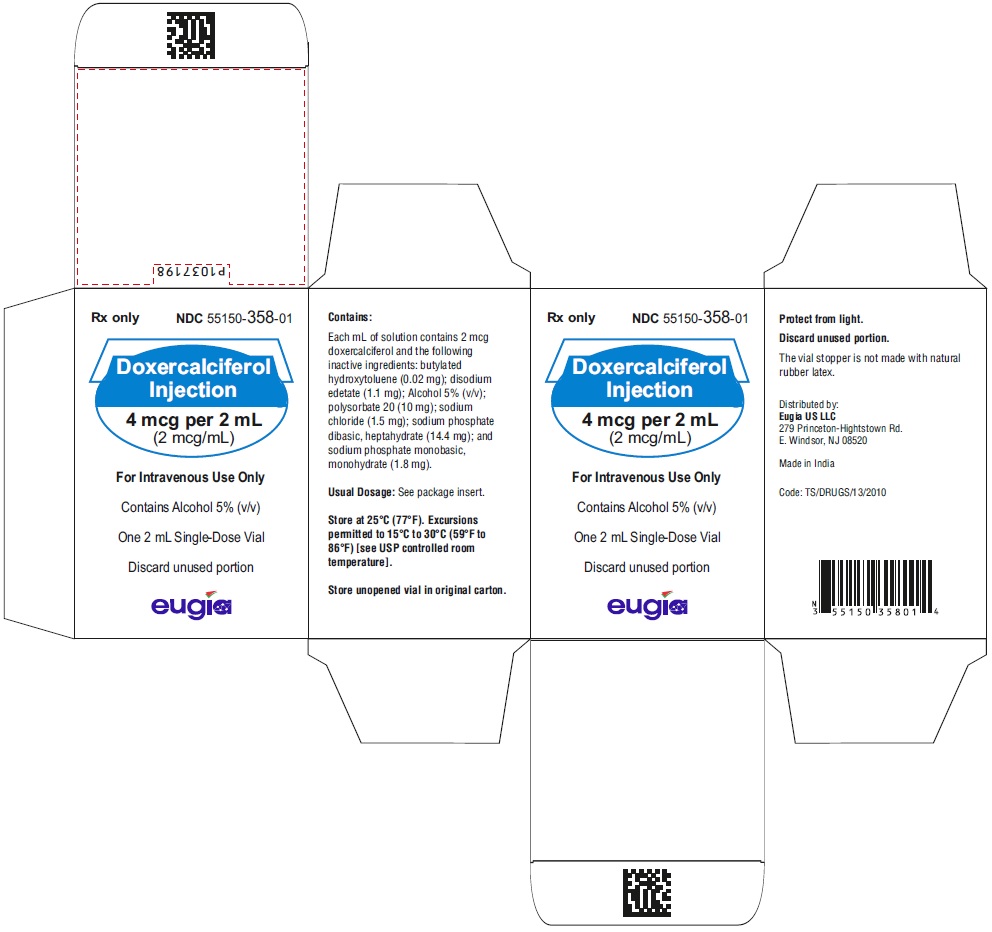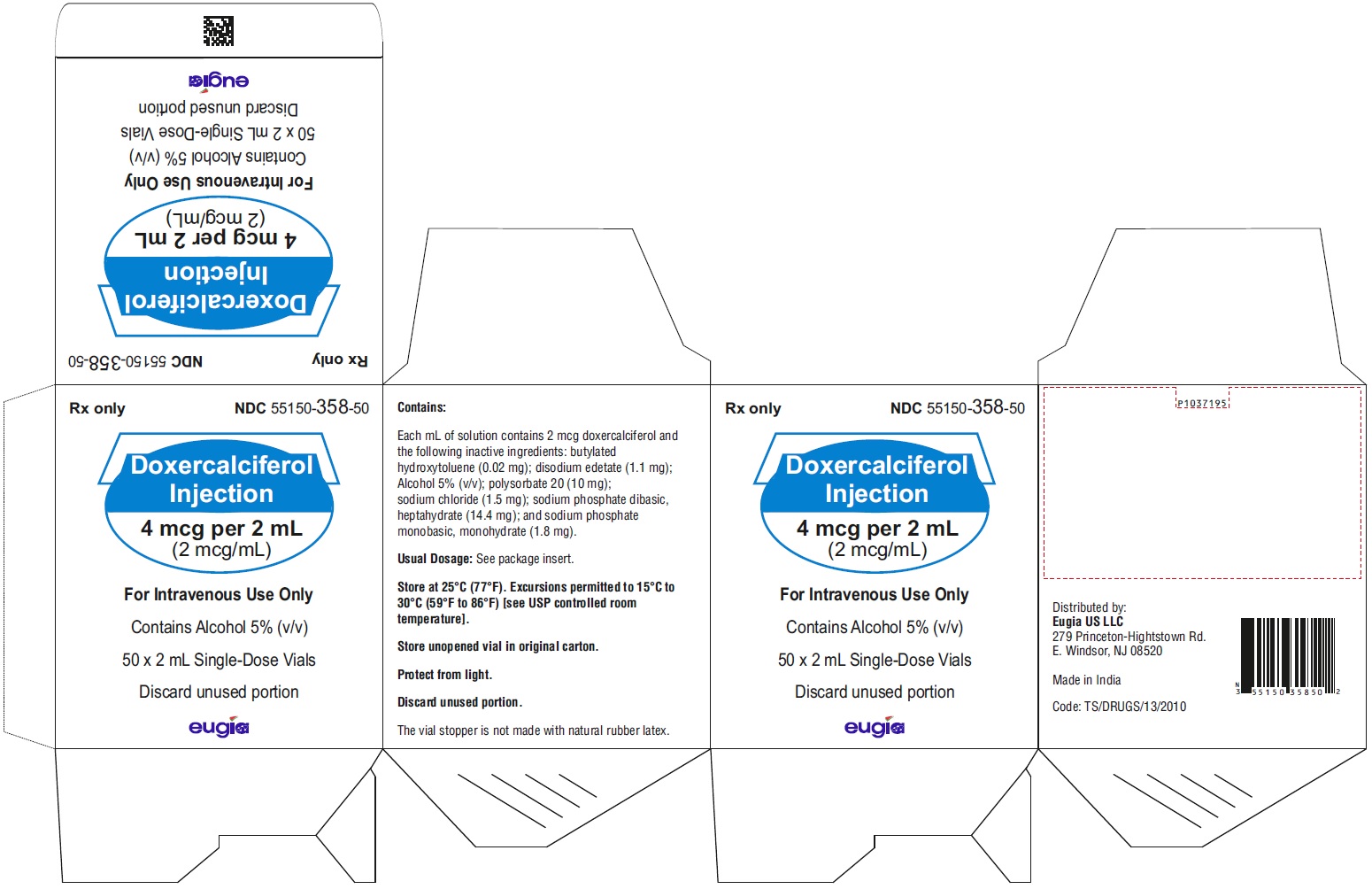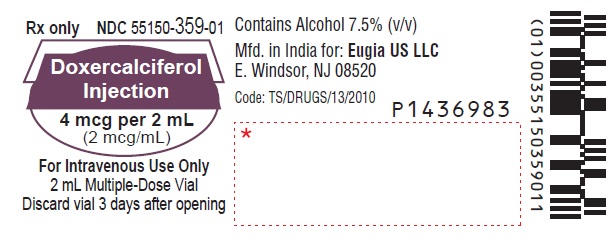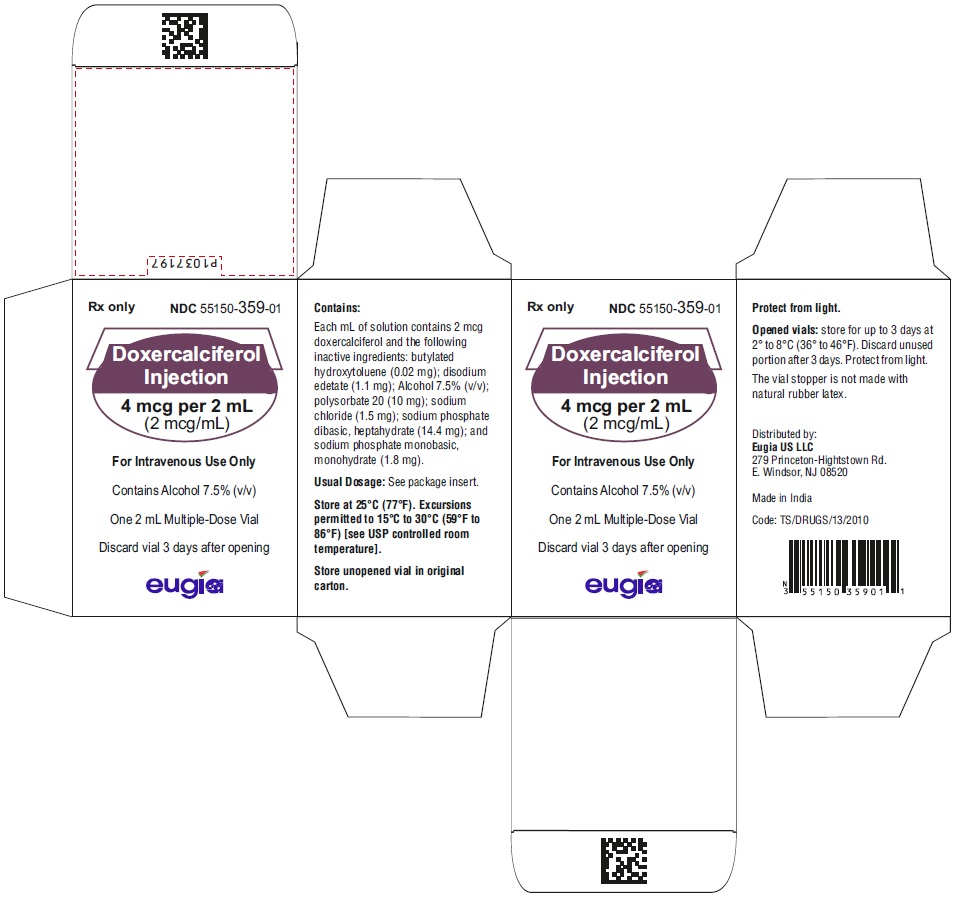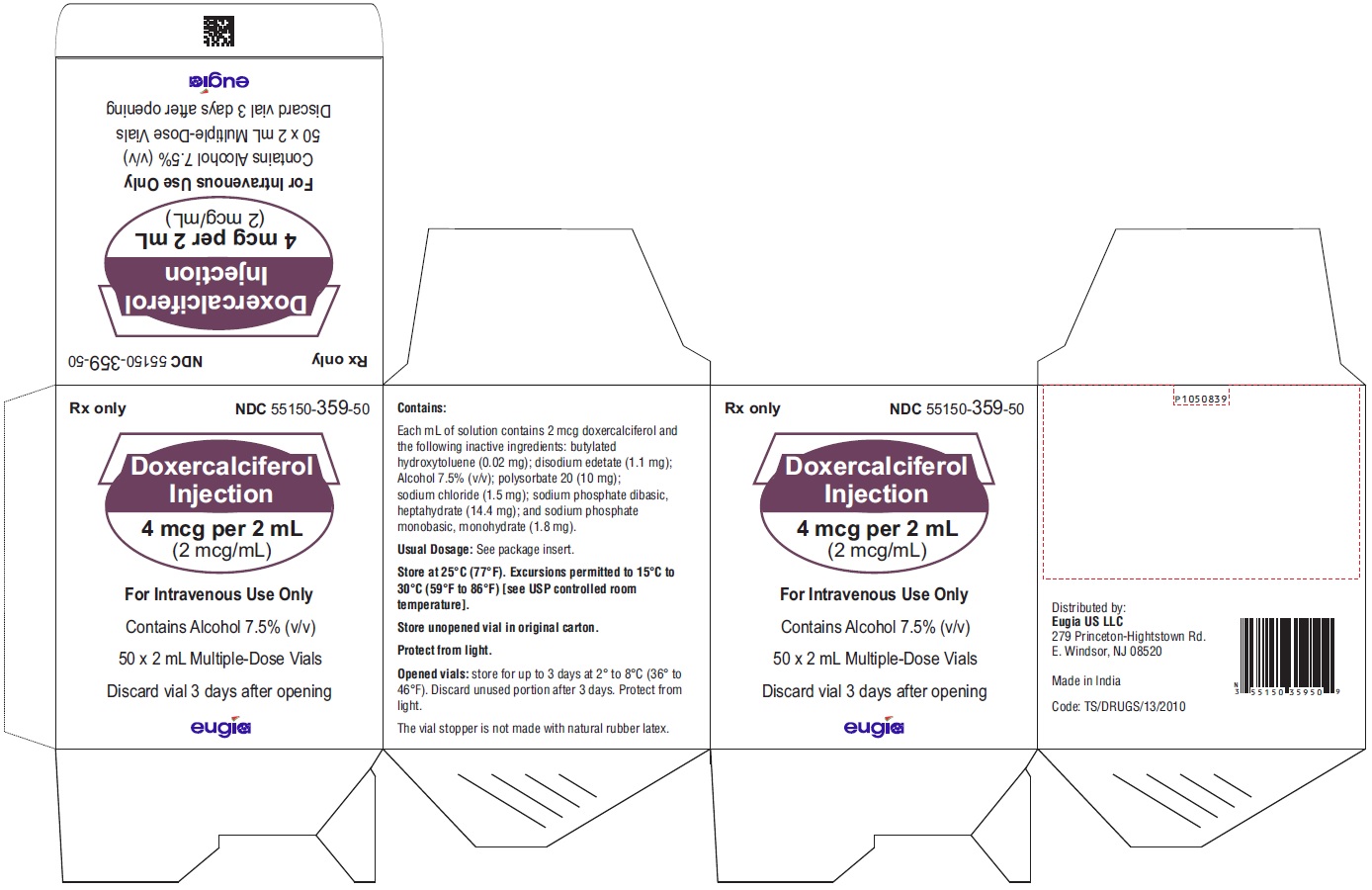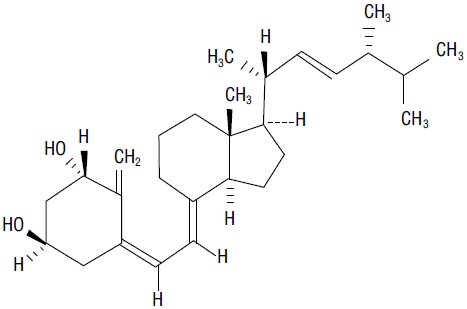 DRUG LABEL: Doxercalciferol
NDC: 55150-357 | Form: INJECTION, SOLUTION
Manufacturer: Eugia US LLC
Category: prescription | Type: Human Prescription Drug Label
Date: 20251023

ACTIVE INGREDIENTS: DOXERCALCIFEROL 2 ug/1 mL
INACTIVE INGREDIENTS: BUTYLATED HYDROXYTOLUENE; EDETATE DISODIUM; ALCOHOL; POLYSORBATE 20; SODIUM CHLORIDE; SODIUM PHOSPHATE, DIBASIC, HEPTAHYDRATE; SODIUM PHOSPHATE, MONOBASIC, MONOHYDRATE

HIGHLIGHTS OF PRESCRIBING INFORMATION

These highlights do not include all the information needed to use DOXERCALCIFEROL INJECTION safely and effectively. See full prescribing information for DOXERCALCIFEROL INJECTION.
DOXERCALCIFEROL injection, for intravenous use
Initial U.S. Approval: 1999

1 INDICATIONS AND USAGE

Doxercalciferol is a synthetic vitamin D2 analog:

- Doxercalciferol injection is indicated for the treatment of secondary hyperparathyroidism in adult patients with chronic kidney disease (CKD) on dialysis. (1)

2 DOSAGE AND ADMINISTRATION

- Before initiating treatment, ensure serum calcium is not above the upper limit of normal. (2.1)
- Dosage for doxercalciferol injection in patients with CKD on dialysis: Initiate dosing at 4 mcg by bolus intravenous administration three times weekly at the end of dialysis (no more frequently than every other day). Maximum dose is 18 mcg weekly. (2.4)
- Target the maintenance dose of doxercalciferol injection to intact parathyroid hormone (PTH) levels within the desired therapeutic range and serum calcium within normal limits. (2)
- See Full Prescribing Information for dose titration, laboratory monitoring, and important administration instructions. (2)

3 DOSAGE FORMS AND STRENGTHS

- Injection: (3)
  - 2 mcg per mL single-dose vial
  - 4 mcg per 2 mL (2 mcg/mL) single-dose vial
  - 4 mcg per 2 mL (2 mcg/mL) multiple-dose vial

4 CONTRAINDICATIONS

- Hypercalcemia (4)
- Vitamin D toxicity (4)
- Know hypersensitivity to doxercalciferol or any of the inactive ingredients of doxercalciferol injection (4)

5 WARNINGS AND PRECAUTIONS

- Hypercalcemia: Can occur during treatment with doxercalciferol and can lead to cardiac arrhythmias and seizures. Severe hypercalcemia may require emergency attention. Risk may be increased when used concomitantly with high dose calcium preparations, thiazide diuretics, or vitamin D compounds. Monitor serum calcium prior to initiation and during treatment and adjust dose accordingly. (2, 5.1)
- Digitalis Toxicity: Hypercalcemia increases the risk of digitalis toxicity. In patients using digitalis compounds, monitor serum calcium and patients for signs and symptoms of digitalis toxicity. Increase frequency of monitoring when initiating or adjusting the dose of doxercalciferol. (5.2)
- Serious Hypersensitivity Reactions: Anaphylaxis, with symptoms of angioedema, hypotension, unresponsiveness, chest discomfort, shortness of breath, and cardiopulmonary arrest, has been reported in hemodialysis patients after administration of doxercalciferol. Monitor patients upon treatment initiation for hypersensitivity reactions. Should a reaction occur, discontinue and treat. (5.3)
- Adynamic Bone Disease: May develop and increase risk of fractures if intact PTH levels are suppressed to abnormally low levels. Monitor intact PTH levels to avoid oversuppression and adjust dose if needed. (5.4)

6 ADVERSE REACTIONS

The most common adverse reactions in patients with CKD on dialysis (incidence >5%) were headache, malaise, edema, nausea/vomiting, dyspnea, dizziness, pruritus, and bradycardia. (6.1)
To report SUSPECTED ADVERSE REACTIONS, contact Eugia US LLC at 1-866-850-2876 or FDA at 1-800-FDA-1088 or www.fda.gov/medwatch.

7 DRUG INTERACTIONS

- Cytochrome P450 inhibitors: Formation of the active doxercalciferol moiety may be hindered and may necessitate dosage adjustment. Monitor intact PTH and serum calcium concentrations closely. (7)
- Enzyme inducers: Formation of the active doxercalciferol moiety may be affected and may necessitate dosage adjustment. Monitor intact PTH and serum calcium concentrations closely. (7)
- Magnesium-containing products: Combined use may cause hypermagnesemia. Monitor serum magnesium concentrations more frequently and adjust dose as needed. (7)

FULL PRESCRIBING INFORMATION

1 INDICATIONS AND USAGE

- Doxercalciferol injection is indicated for the treatment of secondary hyperparathyroidism in adult patients with chronic kidney disease (CKD) on dialysis.

2 DOSAGE AND ADMINISTRATION

2.1 Prior to Initiation of Doxercalciferol Injection

- Ensure serum calcium is not above the upper limit of normal before initiating treatment with doxercalciferol injection [see Warnings and Precautions (5.1)].

2.4 Important Administration Instructions for Doxercalciferol Injection

- Administer doxercalciferol injection intravenously as a bolus dose at the end of dialysis.
- Inspect doxercalciferol injection visually prior to administration; the solution should appear clear and colorless. Do not use if the solution is not clear or particles are present.
- After initial vial use:
  - discard unused portion of the single-dose vial;
  - store opened multiple-dose vial for up to 3 days at 2°C to 8°C (36°F to 46°F). Discard unused portion of multiple-dose vial after 3 days [see How Supplied/Storage and Handling (16)].

2.5 Dosage Recommendations for Doxercalciferol Injection in Patients with CKD on Dialysis

- Initiate doxercalciferol injection at a dose of 4 mcg given by bolus intravenous administration three times weekly at the end of dialysis (no more frequently than every other day).
- Target the maintenance dose of doxercalciferol injection to intact parathyroid hormone (PTH) levels within the desired therapeutic range and serum calcium within normal limits.
- Monitor serum calcium, phosphorus, and intact PTH levels weekly after initiation of therapy or dose adjustment.
- Titrate the dose of doxercalciferol injection based on intact PTH. The dose may be increased at 8-week intervals by 1 mcg to 2 mcg if intact PTH is not lowered by 50% and fails to reach the target range. The maximum dose is 18 mcg weekly. Prior to raising the dose, ensure serum calcium is within normal limits.
- Suspend or decrease the dose if intact PTH is persistently and abnormally low to reduce the risk of adynamic bone disease [see Warnings and Precautions (5.4)] or if serum calcium is consistently above the normal range to reduce the risk of hypercalcemia [see Warnings and Precautions (5.1)]. If suspended, the drug should be restarted one week later at a dose that is at least 1 mcg lower.

2.6 Drug Interactions that May Require Dosage Adjustments of Doxercalciferol Injection

- Increased monitoring of serum calcium and dose adjustment of doxercalciferol injection may be necessary when given concomitantly with drugs that may increase the risk of hypercalcemia [see Drug Interactions (7)].
- Increased monitoring of both serum calcium and intact PTH as well as dose adjustment of doxercalciferol injection may be necessary when given concomitantly with cytochrome P450 inhibitors or enzyme inducers [see Drug Interactions (7)].

3 DOSAGE FORMS AND STRENGTHS

Injection: clear and colorless aqueous solution available as follows:

- 2 mcg per mL single-dose vial
- 4 mcg per 2 mL (2 mcg/mL) single-dose vial
- 4 mcg per 2 mL (2 mcg/mL) multiple-dose vial

4 CONTRAINDICATIONS

Doxercalciferol is contraindicated in patients with:

- Hypercalcemia [see Warnings and Precautions (5.1)]
- Vitamin D toxicity [see Warnings and Precautions (5.1)]
- Known hypersensitivity to doxercalciferol or any of the inactive ingredients of doxercalciferol injection; serious hypersensitivity reactions including anaphylaxis and angioedema have been reported [see Warnings and Precautions (5.3), Adverse Reactions (6.2)].

5 WARNINGS AND PRECAUTIONS

5.1 Hypercalcemia

Hypercalcemia may occur during doxercalciferol treatment. Acute hypercalcemia may increase the risk of cardiac arrhythmias and seizures and may potentiate the effect of digitalis on the heart [see Warnings and Precautions (5.2)]. Chronic hypercalcemia can lead to generalized vascular calcification and other soft-tissue calcification. Severe hypercalcemia may require emergency attention.

Hypercalcemia may be exacerbated by concomitant administration of high doses of calcium-containing preparations, thiazide diuretics, or other vitamin D compounds [see Drug Interactions (7)]. In addition, high intake of calcium and phosphate concomitantly with vitamin D compounds may lead to hypercalciuria and hyperphosphatemia. Patients with a history of hypercalcemia prior to initiating therapy may be at increased risk for development of hypercalcemia with doxercalciferol. In these circumstances, frequent serum calcium monitoring and doxercalciferol dose adjustments may be required.

When initiating doxercalciferol or adjusting doxercalciferol dose, measure serum calcium frequently (weekly in patients with CKD on dialysis). Once a maintenance dose has been established, measure serum calcium monthly for 3 months and then every 3 months. If hypercalcemia occurs, reduce the dose or discontinue doxercalciferol until serum calcium is normal [see Dosage and Administration (2)].

Inform patients about the symptoms of elevated calcium (feeling tired, difficulty thinking clearly, loss of appetite, nausea, vomiting, constipation, increased thirst, increased urination and weight loss) and instruct them to report new or worsening symptoms when they occur.

5.2 Digitalis Toxicity

Doxercalciferol can cause hypercalcemia [see Warnings and Precautions (5.1)] which increases the risk of digitalis toxicity. In patients using doxercalciferol concomitantly with digitalis compounds, monitor both serum calcium and patients for signs and symptoms of digitalis toxicity. Increase the frequency of monitoring when initiating or adjusting the dose of doxercalciferol [see Drug Interactions (7)].

5.3 Serious Hypersensitivity Reactions

Serious hypersensitivity reactions, including fatal outcome, have been reported post marketing in patients on hemodialysis following administration of doxercalciferol injection. Hypersensitivity reactions include anaphylaxis with symptoms of angioedema (involving face, lips, tongue and airways), hypotension, unresponsiveness, chest discomfort, shortness of breath, and cardiopulmonary arrest. These reactions may occur separately or together.
Monitor patients receiving doxercalciferol upon initiation of treatment for hypersensitivity reactions. Should a hypersensitivity reaction occur, discontinue doxercalciferol, monitor and treat if indicated [see Contraindications (4)].

5.4 Adynamic Bone Disease

Adynamic bone disease with subsequent increased risk of fractures may develop if intact PTH levels are suppressed by doxercalciferol to abnormally low levels. Monitor intact PTH levels to avoid oversuppression and adjust the doxercalciferol dose, if needed [see Dosage and Administration (2)].

6 ADVERSE REACTIONS

The following adverse reactions are discussed in greater detail in another section of the label:

- Hypercalcemia [see Warnings and Precautions (5.1)]
- Serious Hypersensitivity Reactions [see Warnings and Precautions (5.3)]
- Adynamic Bone Disease [see Warnings and Precautions (5.4)]

6.1 Clinical Trials Experience

Because clinical trials are conducted under widely varying conditions, adverse reaction rates observed in the clinical trials of a drug cannot be directly compared to rates in the clinical trials of another drug and may not reflect the rates observed in practice.
Doxercalciferol Capsules
Adverse reactions in patients with CKD on dialysis
Doxercalciferol capsules have been evaluated in two placebo-controlled, double-blind studies in patients with CKD on hemodialysis. Patients were treated with doxercalciferol capsules (n=61) or placebo (n=61). After randomization to two groups, eligible patients underwent an 8-week washout period during which no vitamin D derivatives were administered to either group. Subsequently, all patients received doxercalciferol capsules in an open-label fashion for 16 weeks followed by a double-blind period of 8 weeks during which patients received either doxercalciferol capsules or placebo. Adverse reactions occurring in the doxercalciferol capsule groups at a frequency of 2% or greater, and more frequently than in the placebo group are presented in Table 2.

Table 2: Adverse Reactions Occurring in ≥2% Doxercalciferol Capsule-Treated Patients with CKD on Dialysis and Greater than Placebo in Two Double-Blind Clinical Studies
Adverse Reaction* | Doxercalciferol (n=61) % | Placebo (n=61) %
Edema | 34 | 21
Malaise | 28 | 20
Headache | 28 | 18
Nausea/Vomiting | 21 | 20
Dizziness | 12 | 10
Dyspnea | 12 | 7
Pruritus | 8 | 7
Bradycardia | 7 | 5
Anorexia | 5 | 3
Dyspepsia | 5 | 2
Arthralgia | 5 | 0
Weight increase | 5 | 0
Abscess | 3 | 0
Sleep disorder | 3 | 0
* A patient who reported the same medical term more than once was counted only once for that medical term.

Doxercalciferol Injection
Adverse reactions in patients with CKD on hemodialysis
Doxercalciferol injection has been studied in 70 patients with CKD on hemodialysis in two 12-week, open-label, single-arm, multicenter studies [see Clinical Studies (14.3)]. The incidence of hypercalcemia and hyperphosphatemia increased during therapy with doxercalciferol injection. Patients with higher pretreatment serum levels of calcium (>10.5 mg/dL) or phosphorus (>6.9 mg/dL) were more likely to experience hypercalcemia or hyperphosphatemia.
There was no placebo group included in the studies of doxercalciferol injection. Adverse reactions in patients with CKD on hemodialysis receiving doxercalciferol injection are expected to be similar to those reported in placebo-controlled studies of doxercalciferol capsules presented in Table 2.

6.2 Postmarketing Experience

The following adverse reactions have been identified during postapproval use of doxercalciferol. Because these reactions are reported voluntarily from a population of uncertain size, it is not always possible to estimate their frequency or to establish a causal relationship to drug exposure.
Hypersensitivity reactions, including fatal outcome, have been reported in patients on hemodialysis following administration of doxercalciferol injection. Hypersensitivity reactions include anaphylaxis with symptoms of angioedema (involving face, lips, tongue and airways), hypotension, unresponsiveness, chest discomfort, shortness of breath, cardiopulmonary arrest, pruritus, and skin burning sensation.

7 DRUG INTERACTIONS

Table 3 includes clinically significant drug interactions with doxercalciferol.

Table 3: Clinically Significant Drug Interactions with Doxercalciferol Injection
Drugs that May Increase the Risk of Hypercalcemia
Clinical Impact | Concomitant administration of high doses of calcium-containing preparations or other vitamin D compounds may increase the risk of hypercalcemia. Thiazide diuretics are known to induce hypercalcemia by reducing excretion of calcium in the urine.
Examples | Calcium-containing products, other vitamin D compounds or thiazide diuretics
Intervention | Monitor serum calcium concentrations more frequently and adjust doxercalciferol dose as needed [see Warnings and Precautions (5.1)].
Digitalis Compounds
Clinical Impact | Doxercalciferol can cause hypercalcemia which can potentiate the risk of digitalis toxicity.
Intervention | Monitor patients for signs and symptoms of digitalis toxicity and increase frequency of serum calcium monitoring when initiating or adjusting the dose of doxercalciferol in patients receiving digitalis compounds [see Warnings and Precautions (5.2)].
Cytochrome P450 Inhibitors
Clinical Impact | Doxercalciferol is activated by CYP 27 in the liver. Cytochrome P450 inhibitors may inhibit the 25-hydroxylation of doxercalciferol and thus reduce the formation of active doxercalciferol moiety [see Clinical Pharmacology (12.3)].
Examples | Ketoconazole and erythromycin
Intervention | If a patient initiates or discontinues therapy with a cytochrome P450 inhibitor, dose adjustment of doxercalciferol may be necessary. Monitor intact PTH and serum calcium concentrations closely.
Enzyme Inducers
Clinical Impact | Doxercalciferol is activated by CYP 27 in the liver. Enzyme inducers may affect the 25-hydroxylation of doxercalciferol [see Clinical Pharmacology (12.3)].
Examples | Glutethimide and phenobarbital
Intervention | If a patient initiates or discontinues therapy with an enzyme inducer, dose adjustment of doxercalciferol may be necessary. Monitor intact PTH and serum calcium concentrations closely.
Magnesium-containing Products
Clinical Impact | Concomitant administration of doxercalciferol and high doses of magnesium-containing products may increase the risk of hypermagnesemia.
Examples | Magnesium-containing products such as antacids
Intervention | Avoid use of magnesium-containing products and doxercalciferol in patients on chronic renal dialysis.

8 USE IN SPECIFIC POPULATIONS

8.1 Pregnancy

Risk Summary
The limited available data with doxercalciferol in pregnant women are insufficient to identify a drug-associated risk for major birth defects, miscarriage or adverse maternal or fetal outcomes. There are risks to the mother and fetus associated with chronic kidney disease in pregnancy [see Clinical Considerations]. In reproduction studies in rats and rabbits administered doxercalciferol during organogenesis at up to 20 mcg/kg/day and 0.1 mcg/kg/day, respectively (approximately 25 times (rats) and less than (rabbits) the maximum recommended human oral dose of 60 mcg/week based on mcg/m^2 body surface area), no adverse developmental effects were observed [see Data].
The estimated background risk of major birth defects and miscarriage for the indicated population is unknown. In the U.S. general population, the estimated background risk of major birth defects and miscarriage in clinically recognized pregnancies is 2% to 4% and 15% to 20%, respectively.

Clinical Considerations

Disease-associated maternal and/or embryo/fetal risk
Chronic kidney disease in pregnancy increases the risk for maternal hypertension and preeclampsia, miscarriage, preterm delivery polyhydramnios, stillbirth, and low-birth-weight infants.

Data

Animal data
There were no adverse effects on fetal development when doxercalciferol was administered at doses up to 20 mcg/kg/day in pregnant rats or doses up to 0.1 mcg/kg/day in pregnant rabbits during the period of organogenesis.

8.2 Lactation

Risk Summary
There is no information available on the presence of doxercalciferol in human milk, the effects of the drug on the breastfed infant, or the effects of the drug on milk production. Infants exposed to doxercalciferol through breast milk should be monitored for signs and symptoms of hypercalcemia [see Clinical Considerations].
The developmental and health benefits of breastfeeding should be considered along with the mother’s clinical need for doxercalciferol and any potential adverse effects on the breastfed child from doxercalciferol or from the underlying maternal condition.

Clinical Considerations

Infants exposed to doxercalciferol injection through breast milk should be monitored for signs and symptoms of hypercalcemia, including seizures, vomiting, constipation and weight loss. Monitoring of serum calcium in the infant should be considered.

8.4 Pediatric Use

Safety and efficacy of doxercalciferol in pediatric patients have not been established.

8.5 Geriatric Use

Clinical studies of doxercalciferol did not include sufficient numbers of patients 65 years or over to determine whether they respond differently from younger subjects. In general, dose selection for an elderly patient should be cautious, usually starting at the low end of the dosing range, reflecting the greater frequency of decreased hepatic or cardiac function, and of concomitant disease or other drug therapy.

8.6 Hepatic Impairment

Patients with hepatic impairment may not metabolize doxercalciferol appropriately. More frequent monitoring of intact PTH, calcium, and phosphorus levels should be done in patients with hepatic impairment.

10 OVERDOSAGE

Overdosage of doxercalciferol may lead to hypercalcemia, hypercalciuria, and hyperphosphatemia [see Warnings and Precautions (5.1)]. The treatment of acute overdosage should consist of supportive measures and discontinuation of doxercalciferol administration. Serum calcium levels should be measured until normal.
Based on similarities between doxercalciferol and its active metabolite, 1α,25-(OH)2D2, it is expected that doxercalciferol is not removed from the blood by dialysis.

11 DESCRIPTION

Doxercalciferol injection contains doxercalciferol, which is a synthetic vitamin D2 analog. Doxercalciferol undergoes metabolic activation in vivo to form 1α,25-dihydroxyvitamin D2 (1α,25-(OH)2D2), a naturally occurring, biologically active form of vitamin D2.
Doxercalciferol, USP is a white to off-white crystallized powder with a calculated molecular weight of 412.66 and a molecular formula of C28H44O2. It is soluble in oils and organic solvents, but is relatively insoluble in water. Chemically, doxercalciferol is (1α,3β,5Z,7E,22E)-9,10-secoergosta-5,7,10(19),22-tetraene-1,3-diol. The structural formula is:
Injection
Doxercalciferol injection 1 mL single-dose vials contain 2 mcg/mL of doxercalciferol. Doxercalciferol injection 2 mL single-dose vials contain 4 mcg/2 mL (2 mcg/mL) of doxercalciferol. Each milliliter (mL) of solution contains 2 mcg doxercalciferol and the following inactive ingredients: butylated hydroxytoluene (0.02 mg); disodium edetate (1.1 mg); ethanol, 100% (0.05 mL); polysorbate 20 (10 mg); sodium chloride (1.5 mg); sodium phosphate dibasic, heptahydrate (14.4 mg); and sodium phosphate monobasic, monohydrate (1.8 mg).
Doxercalciferol injection 2 mL multiple-dose vials contain 4 mcg/2 mL (2 mcg/mL) of doxercalciferol. Each milliliter (mL) of solution contains 2 mcg doxercalciferol and the following inactive ingredients: butylated hydroxytoluene (0.02 mg); disodium edetate (1.1 mg); ethanol, 100% (0.075 mL); polysorbate 20 (10 mg); sodium chloride (1.5 mg); sodium phosphate dibasic, heptahydrate (14.4 mg); and sodium phosphate monobasic, monohydrate (1.8 mg).

12 CLINICAL PHARMACOLOGY

12.1 Mechanism of Action

Doxercalciferol is a synthetic vitamin D2 analog that requires metabolic activation to form the active 1α,25-(OH)2D2 metabolite, which binds to the vitamin D receptor (VDR) to result in the selective activation of vitamin D responsive pathways. Vitamin D and doxercalciferol have been shown to reduce PTH levels by inhibiting PTH synthesis and secretion.

12.3 Pharmacokinetics

Absorption
In healthy volunteers, peak blood levels of 1α,25-(OH)2D2, the major metabolite of doxercalciferol, are attained at 8 hours after a single intravenous dose of doxercalciferol.
Elimination
The mean elimination half-life of 1α,25-(OH)2D2 after an oral dose is approximately 32 to 37 hours with a range of up to 96 hours.
Metabolism
Doxercalciferol is activated by CYP 27 in the liver to form 1α,25-(OH)2D2 (major metabolite) and 1α,24-dihydroxyvitamin D2 (minor metabolite). Activation of doxercalciferol does not require the involvement of the kidneys.
Specific Populations
Patients with renal impairment
The mean elimination half-life of 1α,25-(OH)2D2 in patients with end-stage renal disease (ESRD) and in healthy volunteers appears to be similar following an oral dose. Hemodialysis causes a temporary increase in 1α,25- (OH)2D2 mean concentrations, presumably due to volume contraction. 1α,25-(OH)2D2 is not removed from blood during hemodialysis.

13 NONCLINICAL TOXICOLOGY

13.1 Carcinogenesis, Mutagenesis, Impairment of Fertility

In a 104-week carcinogenicity study in rats, there was an increased incidence of benign and malignant adrenal pheochromocytomas in both males and females at oral doses of 0.04, 0.13, and 0.39 mcg/kg/day (less than the maximum recommended human oral dose of 60 mcg/week based on mcg/m^2 body surface area). This increased incidence of pheochromocytomas in rats may be due to altered calcium homeostasis by doxercalciferol. No evidence of genetic toxicity was observed in an in vitro bacterial mutagenicity assay (Ames test) or a mouse lymphoma gene mutation assay. Doxercalciferol caused structural chromatid and chromosome aberrations in an in vitro human lymphocyte clastogenicity assay with metabolic activation. However, doxercalciferol was negative in an in vivo mouse micronucleus clastogenicity assay.
Doxercalciferol had no effect on male or female fertility in rats at oral doses up to 2.5 mcg/kg/day (approximately 3 times the maximum recommended human oral dose of 60 mcg/week based on mcg/m^2 body surface area).

14 CLINICAL STUDIES

14.3 Clinical Studies of Doxercalciferol Injection in Patients with CKD on Dialysis

The safety and effectiveness of Doxercalciferol injection were evaluated in two open-label, single-arm, multicenter clinical studies (Study C and Study D) in a total of 70 patients with CKD on hemodialysis. Patients in Study C were an average age of 54 years (range: 23 to 73), were 50% male, and were 61% African- American, 25% Caucasian, and 14% Hispanic, and had been on hemodialysis for an average of 65 months. Patients in Study D were an average age of 51 years (range: 28 to 76), were 48% male, and 100% African-American and had been on hemodialysis for an average of 61 months. This group of 70 of the 138 patients who had been treated with doxercalciferol capsules in prior clinical studies (Study A and Study B) received doxercalciferol injection in an open-label fashion for 12 weeks following an 8-week washout (control) period. Dosing of doxercalciferol injection was initiated at the rate of 4 mcg administered at the end of each dialysis session (3 times weekly) for a total of 12 mcg per week. The dosage of doxercalciferol was adjusted to achieve intact PTH levels (measured weekly) within a targeted range of 150 pg/mL to 300 pg/mL. The dosage was increased by 2 mcg per dialysis session after 8 weeks of treatment if the intact PTH levels remained above 300 pg/mL and were greater than 50% of baseline levels. The maximum dosage was limited to 18 mcg per week. If at any time during the study intact PTH fell below 150 pg/mL, doxercalciferol injection was immediately suspended and restarted at a lower dosage the following week. Mean weekly doses ranged from 9 mcg to 13 mcg in Study C and ranged from 9 mcg to 12 mcg in Study D.
Fifty-two (74%) of the 70 patients who were treated with doxercalciferol injection achieved intact PTH levels ≤300 pg/mL. Forty-one (59%) of these patients exhibited plasma intact PTH levels ≤300 pg/mL on at least 3 occasions. Thirty-six (51%) patients had plasma intact PTH levels <150 pg/mL on at least one occasion during study participation. Decreases in plasma intact PTH from baseline values were calculated using as baseline the average of the last 3 values obtained during the 8-week washout period and are displayed in Table 6.

Table 6: Intact PTH Summary Data for Patients with CKD on Dialysis Receiving Doxercalciferol Injection in Studies C and D
Intact PTH Level | Study C (n=28) | Study D (n=42) | Combined Protocols (n=70)
Baseline (Mean of Weeks -2, -1, and 0)
Mean (SE) | 698 (60) | 762 (65) | 736 (46)
Median | 562 | 648 | 634
On-treatment (Week 12*)
Mean (SE) | 406 (63) | 426 (60) | 418 (43)
Median | 311 | 292 | 292
Change from Baseline†
Mean (SE) | -292 (55) | -336 (41) | -318 (33)
Median | -274 | -315 | -304
P-value‡ | 0.004 | 0.001 | <0.001
* Values were carried forward for the two patients on study for 10 weeks
† Treatment intact PTH minus baseline intact PTH
‡ Wilcoxon one-sample test

Doxercalciferol treatment resulted in at least 30% reduction from baseline in mean intact PTH levels during the 12-week open-label treatment period in more than 92% of the 70 treated patients.

16 HOW SUPPLIED/STORAGE AND HANDLING

How Supplied
Doxercalciferol injection is a clear, colorless aqueous solution supplied in 2 mL amber glass vials as follows.

Total Strength per Total Volume | Strength per mL | Flip-off Cap Color | Vial Count per Carton × Total Vial Volume and vial Type | Carton NDC | Vial NDC
2 mcg per mL | 2 mcg/mL | Yellow | 1 × 1 mL single-dose vial | 55150-357-01 | 55150-357-01
2 mcg per mL | 2 mcg/mL | Yellow | 50 × 1 mL single-dose vials | 55150-357-50 | 55150-357-01
4 mcg per 2 mL | 2 mcg/mL | Sky blue | 1 × 2 mL single-dose vial | 55150-358-01 | 55150-358-01
4 mcg per 2 mL | 2 mcg/mL | Sky blue | 50 × 2 mL single-dose vials | 55150-358-50 | 55150-358-01
4 mcg per 2 mL | 2 mcg/mL | Magenta | 1 × 2 mL multiple-dose vial | 55150-359-01 | 55150-359-01
4 mcg per 2 mL | 2 mcg/mL | Magenta | 50 × 2 mL multiple-dose vials | 55150-359-50 | 55150-359-01

Storage and Handling

Dosage Form | Storage temperature | Excursions permitted to | In-use storage
Single-dose vial* | 25°C (77°F) | 15°C to 30°C (59°F to 86°F) [see USP controlled room temperature] | Discard unused portion
Multiple-dose vial* | 25°C (77°F) | 15°C to 30°C (59°F to 86°F) [see USP controlled room temperature] | 2°C to 8°C (36°F to 46°F), Discard 3 days after opening
*Protect from light. Store unopened vial in original carton.

The vial stopper is not made with natural rubber latex.

17 PATIENT COUNSELING INFORMATION

Hypercalcemia
Advise patients to contact a health care provider if they develop symptoms of elevated calcium (e.g. feeling tired, difficulty thinking clearly, loss of appetite, nausea, vomiting, constipation, increased thirst, increased urination and weight loss) [see Warnings and Precautions (5.1)].
Hypersensitivity
Inform patients that hypersensitivity reactions can occur with doxercalciferol [see Warnings and Precautions (5.3)].
Monitoring
Inform patients that they will need routine monitoring of laboratory parameters such as calcium and intact PTH while receiving doxercalciferol. Inform patients that more frequent monitoring is necessary during the initiation of therapy, following dose changes or when potentially interacting medications are started or discontinued [see Dosage and Administration (2), Drug Interactions (7)].
Drug Interactions
Advise patients to inform their physician of all medications, including prescription and nonprescription drugs, and supplements they are taking. Advise patients to also inform their physician that they are receiving doxercalciferol if a new medication is prescribed [see Drug Interactions (7)].
Distributed by:
Eugia US LLC
279 Princeton-Hightstown Rd.
E. Windsor, NJ 08520
Manufactured by:
Eugia Pharma Specialities Limited
Hyderabad - 500032
India

PACKAGE LABEL-PRINCIPAL DISPLAY PANEL-2 mcg per mL - Container Label

Rx only NDC 55150-357-01
Doxercalciferol
Injection
2 mcg per mL
For Intravenous Use Only
1 mL Single-Dose Vial
Discard unused portion

PACKAGE LABEL-PRINCIPAL DISPLAY PANEL-2 mcg per mL - Container-Carton (1 Vial)

Rx only NDC 55150-357-01
Doxercalciferol
Injection
2 mcg per mL
For Intravenous Use Only
Contains Alcohol 5% (v/v)
One 1 mL Single-Dose Vial
Discard unused portion
eugia

PACKAGE LABEL-PRINCIPAL DISPLAY PANEL-2 mcg per mL - Container-Carton (50 Vials)

Rx only NDC 55150-357-50
Doxercalciferol
Injection
2 mcg per mL
For Intravenous Use Only
Contains Alcohol 5% (v/v)
50 x 1 mL Single-Dose Vials
Discard unused portion
eugia

PACKAGE LABEL-PRINCIPAL DISPLAY PANEL-4 mcg per 2 mL (2 mcg/mL) (SDV) - Container Label

Rx only NDC 55150-358-01
Doxercalciferol
Injection
4 mcg per 2 mL
(2 mcg/mL)
For Intravenous Use Only
2 mL Single-Dose Vial
Discard unused portion

PACKAGE LABEL-PRINCIPAL DISPLAY PANEL-4 mcg per 2 mL (2 mcg/mL) (SDV) - Container-Carton (1 Vial)

Rx only NDC 55150-358-01
Doxercalciferol
Injection
4 mcg per 2 mL
(2 mcg/mL)
For Intravenous Use Only
Contains Alcohol 5% (v/v)
One 2 mL Single-Dose Vial
Discard unused portion
eugia

PACKAGE LABEL-PRINCIPAL DISPLAY PANEL-4 mcg per 2 mL (2 mcg/mL) (SDV) - Container-Carton (50 Vials)

Rx only NDC 55150-358-50
Doxercalciferol
Injection
4 mcg per 2 mL
(2 mcg/mL)
For Intravenous Use Only
Contains Alcohol 5% (v/v)
50 x 2 mL Single-Dose Vials
Discard unused portion
eugia

PACKAGE LABEL-PRINCIPAL DISPLAY PANEL-4 mcg per 2 mL (2 mcg/mL) (MDV) - Container Label

Rx only NDC 55150-359-01
Doxercalciferol
Injection
4 mcg per 2 mL
(2 mcg/mL)
For Intravenous Use Only
2 mL Multiple-Dose Vial
Discard vial 3 days after opening

PACKAGE LABEL-PRINCIPAL DISPLAY PANEL-4 mcg per 2 mL (2 mcg/mL) (MDV) - Container-Carton (1 Vial)

Rx only NDC 55150-359-01
Doxercalciferol
Injection
4 mcg per 2 mL
(2 mcg/mL)
For Intravenous Use Only
Contains Alcohol 7.5% (v/v)
One 2 mL Multiple-Dose Vial
Discard vial 3 days after opening
eugia

PACKAGE LABEL-PRINCIPAL DISPLAY PANEL-4 mcg per 2 mL (2 mcg/mL) (MDV) - Container-Carton (50 Vials)

Rx only NDC 55150-359-50
Doxercalciferol
Injection
4 mcg per 2 mL
(2 mcg/mL)
For Intravenous Use Only
Contains Alcohol 7.5% (v/v)
50 x 2 mL Multiple-Dose Vials
Discard vial 3 days after opening
eugia